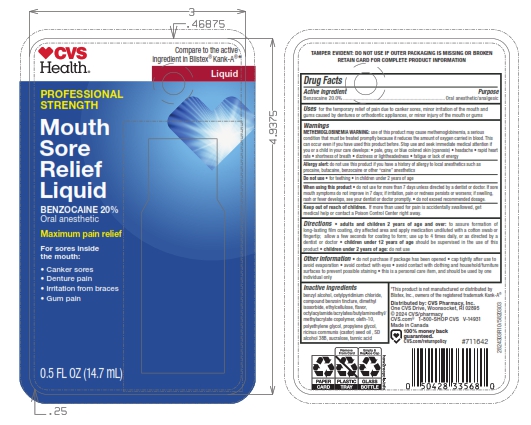 DRUG LABEL: Mouth Sore Relief
NDC: 59779-830 | Form: LIQUID
Manufacturer: CVS Pharmacy
Category: otc | Type: HUMAN OTC DRUG LABEL
Date: 20250930

ACTIVE INGREDIENTS: BENZOCAINE 200 mg/1 g
INACTIVE INGREDIENTS: ALCOHOL; ETHYLCELLULOSES; TANNIC ACID; CETYLPYRIDINIUM CHLORIDE; SUCRALOSE; BENZYL ALCOHOL; PROPYLENE GLYCOL; OLETH-10; DIMETHYL ISOSORBIDE; RICINUS COMMUNIS SEED; POLYETHYLENE GLYCOL 300; BENZOIN, (+/-)

5820303 CVS Mouth Sore Relief

Active ingredient

Benzocaine 20%

Purpose

Oral Anesthetic/Analgesic

Uses

for the temporary relief of pain due to canker sores, minor irritation of the mouth and gums caused by dentures or orthodontic appliances, or minor injury of the mouth or gums

WARNINGS

Methemoglobinemia warning: use of this product may cause methemoglobinemia, a serious condition that must be treated promptly because it reduces the amount of oxygen carried in blood. This can oocur even if you have use this product before. stop ise and seek immediate medical attention if you or a child in you care develops:

- palre, gray, or blue colored skin (cyanosis)
- headache
- rapid heart rate
- shotness of breath
- dizziness or lightheadedness
- fatique or lack of energy

Allergy alert: do not use this product if you have a history of allergy to local anesthetics such as procaine, butacaine, benzocaine or other “caine” anesthetics

Do not use:

- for teething
- in children under 2 years of age

When using this product

- do not use for more than 7 days unless directed by a dentist or doctor. If sore mouth symptoms do not improve in 7 days; if irritation, pain, or redness persists or worsens; f swelling, rash, of fever develops, see your dentist or doctor promptly.

Keep out of reach of children. If more than used for pain is accidentally swallowed, get medical help or contact a Poison Control Center right away.

Directions

- to assure formation of long-lasting film coating, dry affected area and apply medication undiluted with applicator
- allow a few seconds for coating to form
- use up to 4 times daily, or as directed by a dentist or doctor
- children under 12 years of age should be supervised in the use of this product
- children under 2 years of age: consult a dentist or doctor

Other Information

• do not purchase if package has been opened
• cap tightly after use to avoid evaporation
• avoid contact with eyes
• avoid contact with clothing and household/furniture surfaces to prevent possible staining
• this is a personal care item, and should be used by one individual only

Inactive ingredients

Benzyl Alcohol, Cetylpyridinium Chloride, Compound Benzoin Tincture, Dimethyl Isosorbide, Ethylcellulose, Flavor, Octylacrylamide/acrylates/butylaminoethyl/methacrylate Copolymer, Oleth-10, polyethylene glycol, Propylene Glycol, Ricinus Communis (Castor) seed Oil, SD Alcohol 38B, Sucralose,Tannic Acid